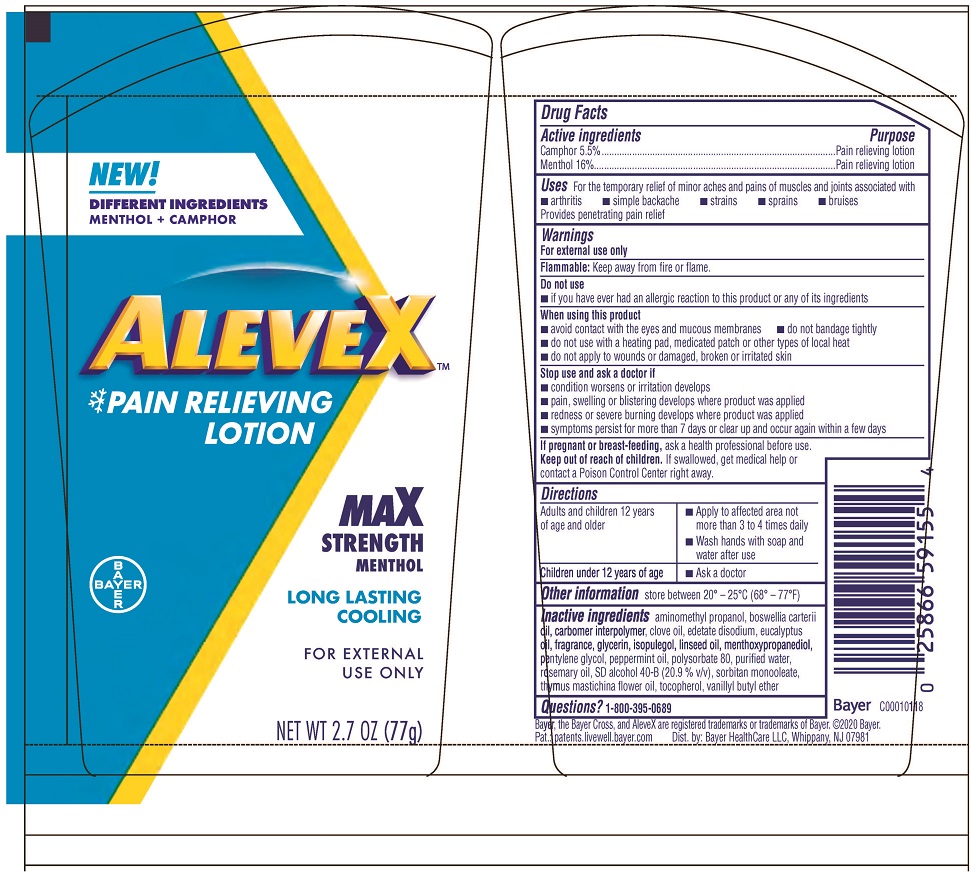 DRUG LABEL: AleveX
NDC: 0280-0063 | Form: LOTION
Manufacturer: Bayer HealthCare LLC
Category: otc | Type: HUMAN OTC DRUG LABEL
Date: 20251204

ACTIVE INGREDIENTS: CAMPHOR (SYNTHETIC) 5.5 mg/1 g; MENTHOL 16 mg/1 g
INACTIVE INGREDIENTS: CARBOMER INTERPOLYMER TYPE A (ALLYL SUCROSE CROSSLINKED); THYMUS MASTICHINA FLOWERING TOP OIL; ALCOHOL; SORBITAN MONOOLEATE; CLOVE OIL; TOCOPHEROL; GLYCERIN; PEPPERMINT OIL; FRANKINCENSE OIL; LINSEED OIL; 3-((L-MENTHYL)OXY)PROPANE-1,2-DIOL; PENTYLENE GLYCOL; WATER; ROSEMARY OIL; VANILLYL BUTYL ETHER; AMINOMETHYLPROPANOL; ISOPULEGOL; EDETATE DISODIUM; EUCALYPTUS OIL; POLYSORBATE 80

AleveX Lotion UI1614388

Drug Facts

AleveX Lotion

Active ingredients
Camphor 5.5%
Menthol 16%

PURPOSE

Pain relieving lotion

Uses

For the temporary relief of minor aches and pains of muscles and joints associated with

- arthritis
- simple backache
- strains
- sprains
- bruises

Provides penetrating pain relief

Warnings

For external use only

Flammable: Keep away from fire or flame.

Do not use

- if you have ever had an allergic reaction to this product or any of its ingredients

When using this product

- avoid contact with the eyes and mucous membranes
- do not bandage tightly
- do not use with a heating pad, medicated patch or other types of local heat
- do not apply to wounds or damaged, broken or irritated skin

Stop use and ask a doctor

- condition worsens or irritation develops
- pain, swelling or blistering develops where product was applied
- redness or severe burning develops where product was applied
- symptoms persist for more than 7 days or clear up and occur again within a few days

PREGNANCY OR BREAST FEEDING

If pregnant or breast-feeding, ask a health professional before use

Keep out of reach of children

If swallowed, get medical help or contact a Poison Control Center right away.

Directions

Adults and children 12 years of age and older | - Apply to affected area not more than 3 to 4 times daily - Wash hands with soap and water after use
Children under 12 years of age | - Ask a Doctor

Other information

store between 20º-25ºC (68º-77ºF)

Inactive ingredients

aminomethyl propanol, boswellia carterii oil, carbomer interpolymer, clove oil, edetate disodium, eucalyptus oil, fragrance, glycerin, isopulegol, linseed oil, menthoxypropanediol, pentylene glycol, peppermint oil, polysorbate 80, purified water, rosemary oil, SD alcohol 40-B (20.9 % v/v), sorbitan monooleate, thymus mastichina flower oil, tocopherol, vanillyl butyl ether

Questions or Comments?

1-800-395-0689

Package label 2.7 oz.

NEW!

DIFFERENT INGREDIENTS

MENTHOL + CAMPHOR

AleveX™

Pain Relieving

Lotion

MAX

STRENGTH

MENTHOL

LONG LASTING

COOLING

FOR EXTERNAL

USE ONLY

NET WT 2.7 OZ (77g)